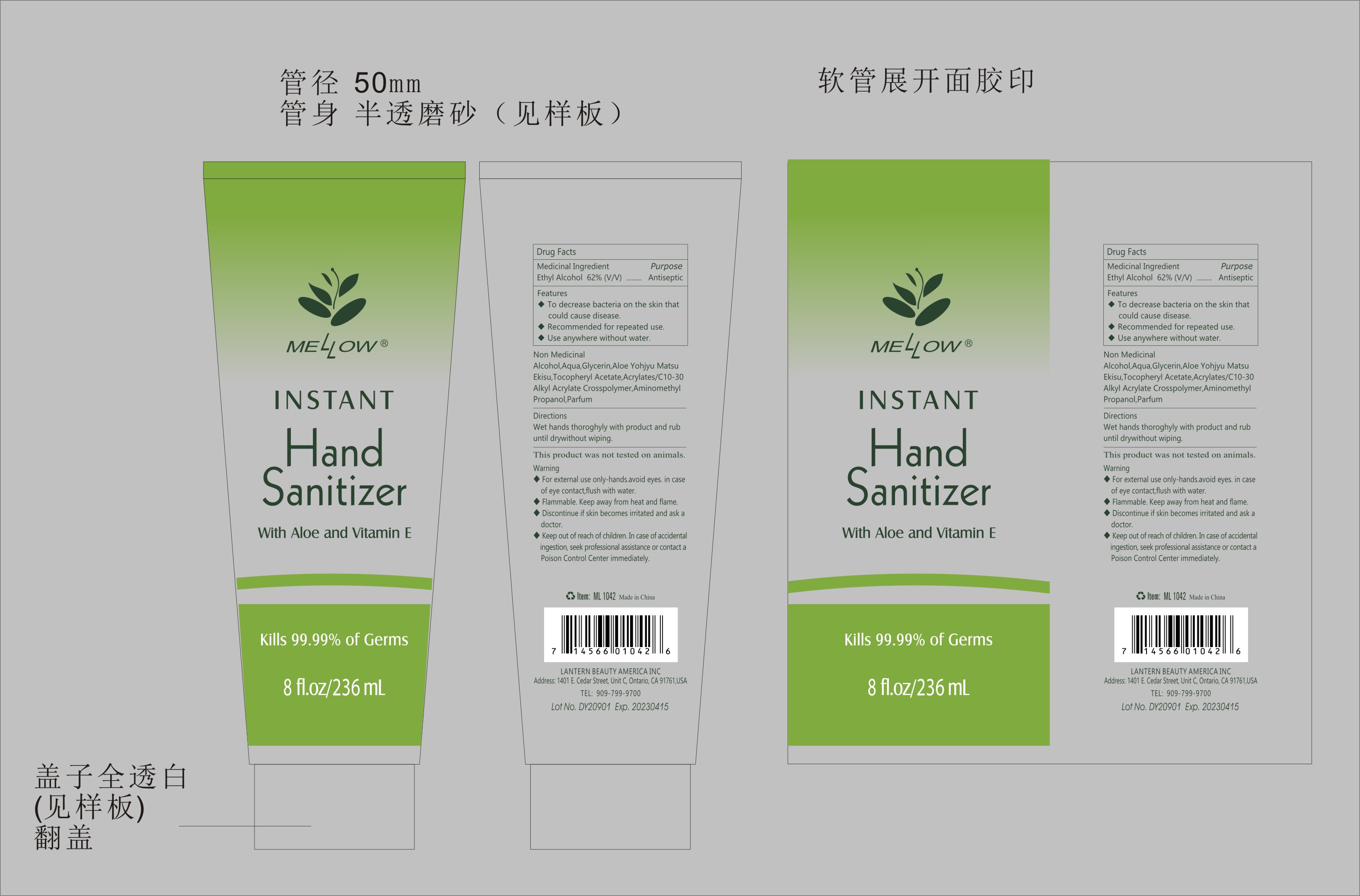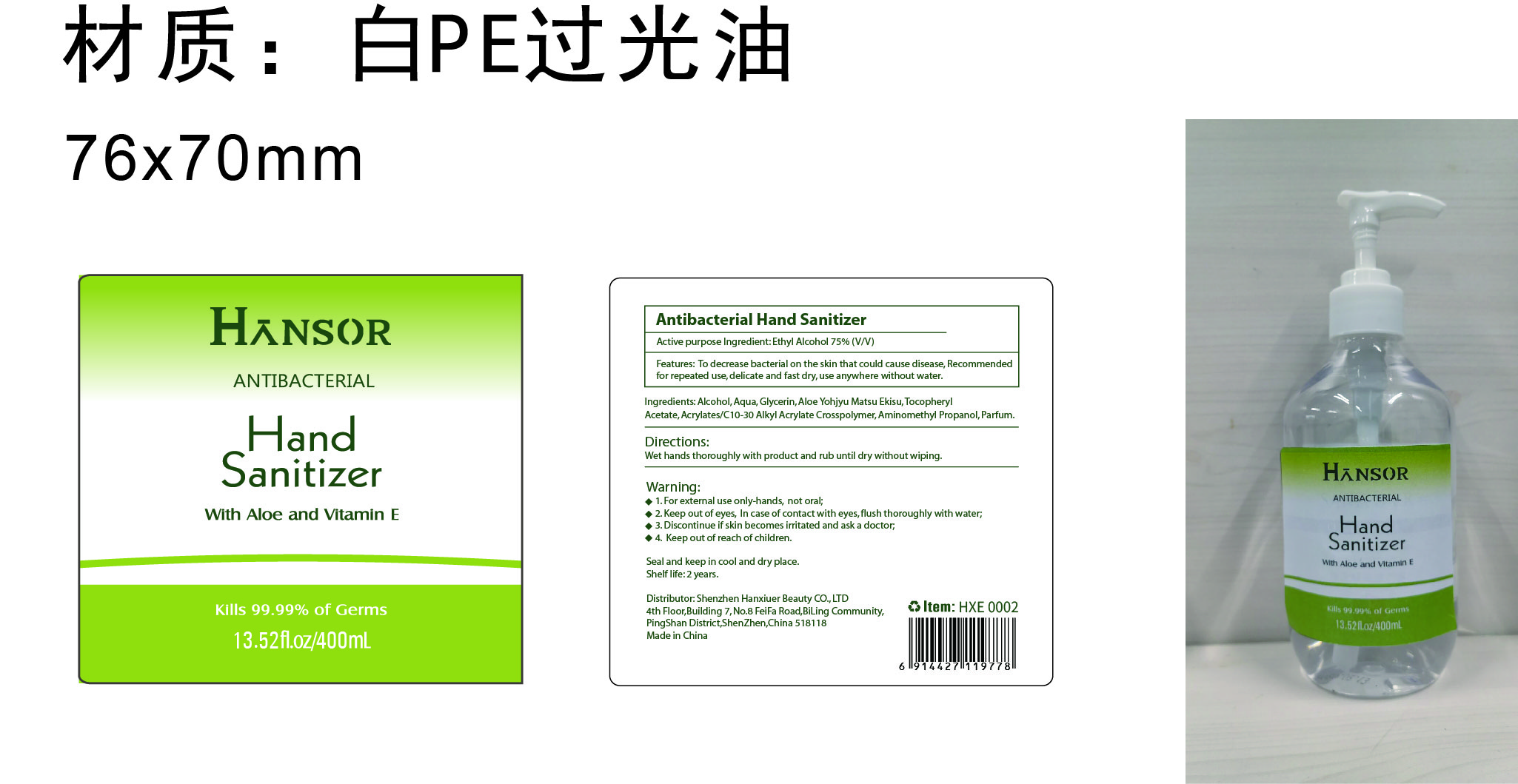 DRUG LABEL: Mellow instant hand sanitizer with aloe and vitamin E 236ml
NDC: 54860-394 | Form: LIQUID
Manufacturer: Shenzhen Lantern Scicence Co Ltd
Category: otc | Type: HUMAN OTC DRUG LABEL
Date: 20220418

ACTIVE INGREDIENTS: ALCOHOL 62 mL/100 mL
INACTIVE INGREDIENTS: CARBOMER INTERPOLYMER TYPE A (ALLYL SUCROSE CROSSLINKED) 0.26 mL/100 mL; ALOE VERA LEAF 0.1 mL/100 mL; .ALPHA.-TOCOPHEROL ACETATE 0.01 mL/100 mL; ALOE 0.15 mL/100 mL; AMINOMETHYLPROPANOL 0.08 mL/100 mL; WATER 37.05 mL/100 mL; GLYCERIN 0.5 mL/100 mL

Mellow instant hand sanitizer with aloe and vitamin E 236ml

Medicical Ingredient

Medicical Ingredient Purpose

Ethyl Alcohol 75%（V/V） Antiseptic

Features

To decrease bacteria on the skin that could cause disease.

DOSAGE AND ADMINISTRATION

Recommended for repeated use.

use anywhere without water.

Warning

WARNINGS AND PRECAUTIONS

For external use only.

Flammable, keep away from heat and flame.

STOP USE

Discontinue if skin becomes irritated and ask a doctor .

Keep out of reach of children. In case of accidental ingestion, seek professional assistance or contact a poson control center immediately.

Non-Medicinal

Water, Glycerin,Aloe Yohjyu Mastu Ekisu,Tocopheryl Acetate,Acrylates/C10-30 Alkyl Acrylate Crosspolymer,Aminomethyl propanol,Parfum.

Directions

Wet hands thoroughly with product and rub until dry without wiping

For children under 6, use only under adult supervision.

Not recommended for infants.

When using this product

keep out of eyes. In case of contact with eyes, flush thoroughly with water.

Do not inhale or ingest.

Avoid contact with broken skin.

Other information

Do not store above 105F.

May discolor some fabrics.

Harmful to wood finishes and plastics.